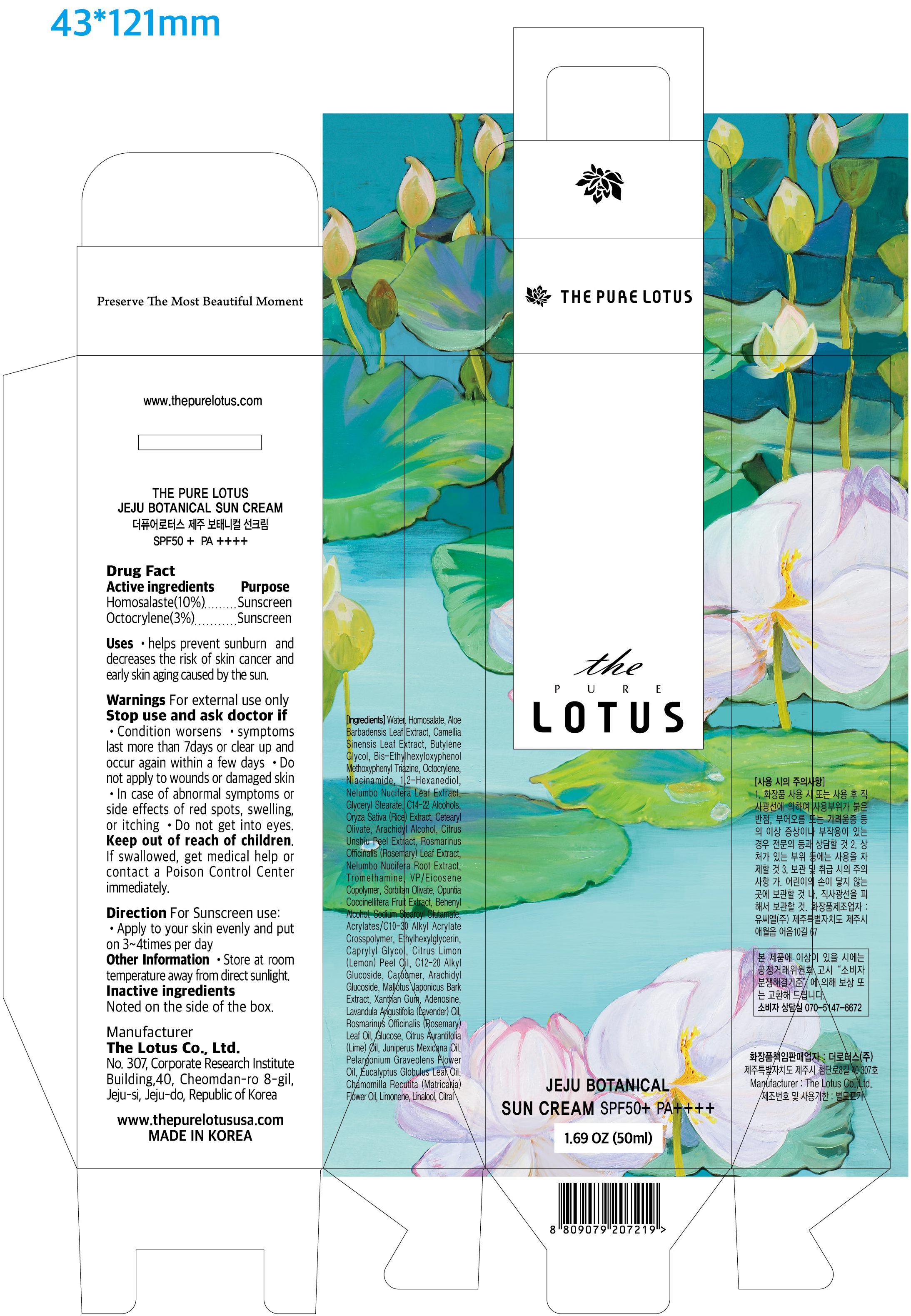 DRUG LABEL: THE PURE LOTUS Jeju Botanical SunCream
NDC: 82235-304 | Form: CREAM
Manufacturer: THE LOTUS Co.,Ltd.
Category: otc | Type: HUMAN OTC DRUG LABEL
Date: 20210928

ACTIVE INGREDIENTS: OCTOCRYLENE 3 g/100 mL; HOMOSALATE 10 g/100 mL
INACTIVE INGREDIENTS: VINYLPYRROLIDONE/EICOSENE COPOLYMER; LIMONENE, (+)-; LEMON OIL; ROSEMARY OIL; CITRAL; LIME OIL; CARBOMER HOMOPOLYMER, UNSPECIFIED TYPE; XANTHAN GUM; ADENOSINE; ALOE VERA LEAF; NELUMBO NUCIFERA LEAF; RICE GERM; ROSEMARY; 1,2-HEXANEDIOL; OPUNTIA COCHENILLIFERA FRUIT; BEMOTRIZINOL; BUTYLENE GLYCOL; NIACINAMIDE; PELARGONIUM GRAVEOLENS FLOWER OIL; EUCALYPTUS OIL; MALLOTUS JAPONICUS BARK; TANGERINE PEEL; WATER; GREEN TEA LEAF; NELUMBO NUCIFERA ROOT; ARACHIDYL ALCOHOL; CAPRYLYL GLYCOL; TROMETHAMINE; CARBOMER INTERPOLYMER TYPE A (55000 CPS); SODIUM STEAROYL GLUTAMATE; ARACHIDYL GLUCOSIDE; GLYCERYL MONOSTEARATE; C14-22 ALCOHOLS; C12-20 ALKYL GLUCOSIDE; ANHYDROUS DEXTROSE; DOCOSANOL; ETHYLHEXYLGLYCERIN; LINALOOL, (+/-)-; LAVENDER OIL; JUNIPERUS DEPPEANA WOOD OIL; CHAMOMILE FLOWER OIL; SORBITAN OLIVATE; CETEARYL OLIVATE

82235-304 THE PURE LOTUS Jeju Botanical Sun Cream

Active ingredients

Homosalaste(10%)

Octocrylene(3%)

Purpose

Sunscreen

Uses

- helps prevent sunburn and decreases the risk of skin cancer and early skin aging caused by the sun.

Warnings

For external use only

Stop use and ask doctor if

- Condition worsens
- symptoms last more than 7days or clear up and occur again within a few days

Do not use

- Do not apply to wounds or damaged skin
- In case of abnormal symptoms or side effects of red spots, swelling, or itching
- Do not get into eyes.

Keep out of reach of children.

If swallowed, get medical help or contact a Poison Control Center immediately.

Direction

For Sunscreen use;

- Apply to your skin evenly and put on 3~4times per day

Other Information

- Store at room temperature away from direct sunlight.

Inactive ingredients

Water, Aloe Barbadensis Leaf Extract, Camellia Sinensis Leaf Extract, Butylene Glycol, Bis-Ethylhexyloxyphenol Methoxyphenyl Triazine, Niacinamide, 1,2-Hexanediol, Nelumbo Nucifera Leaf Extract, Glyceryl Stearate, C14-22 Alcohols, Oryza Sativa (Rice) Extract, Cetearyl Olivate, Arachidyl Alcohol, Citrus Unshiu Peel Extract, Rosmarinus Officinalis (Rosemary) Leaf Extract, Nelumbo Nucifera Root Extract, Tromethamine, VP/Eicosene Copolymer, Sorbitan Olivate, Opuntia Coccinellifera Fruit Extract, Behenyl Alcohol, Sodium Stearoyl Glutamate, Acrylates/C10-30 Alkyl Acrylate Crosspolymer, Ethylhexylglycerin, Caprylyl Glycol, Citrus Limon (Lemon) Peel Oil, C12-20 Alkyl Glucoside, Carbomer, Arachidyl Glucoside, Mallotus Japonicus Bark Extract, Xanthan Gum, Adenosine, Lavandula Angustifolia (Lavender) Oil, Rosmarinus Officinalis (Rosemary) Leaf Oil, Glucose, Citrus Aurantifolia (Lime) Oil, Juniperus Mexicana Oil, Pelargonium Graveolens Flower Oil, Eucalyptus Globulus Leaf Oil, Chamomilla Recutita (Matricaria) Flower Oil, Limonene, Linalool, Citral.